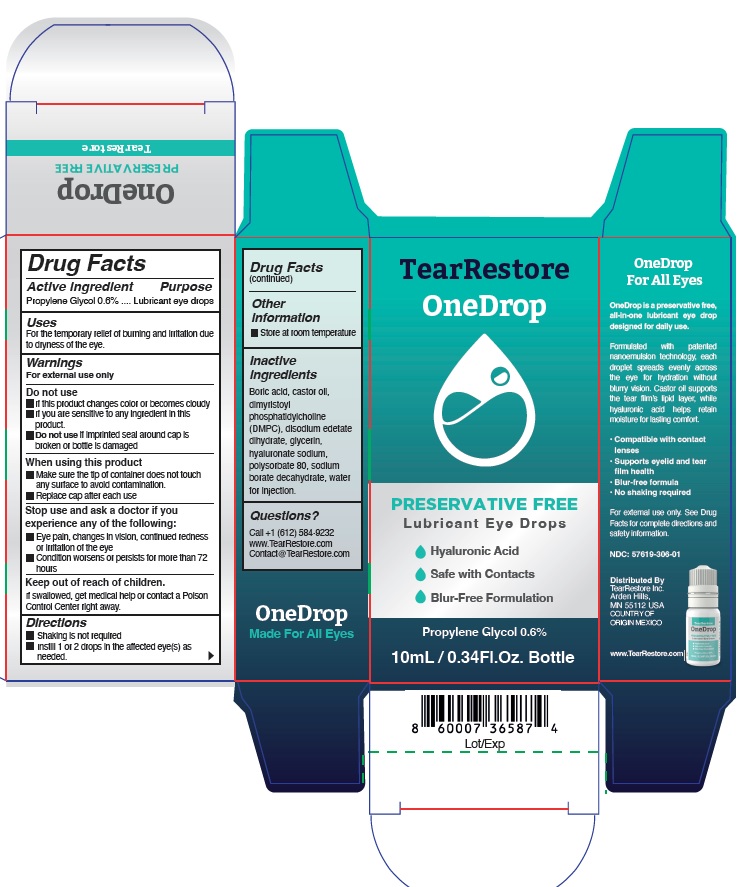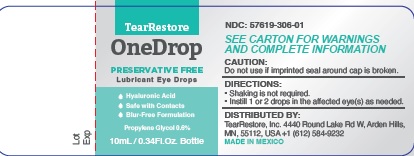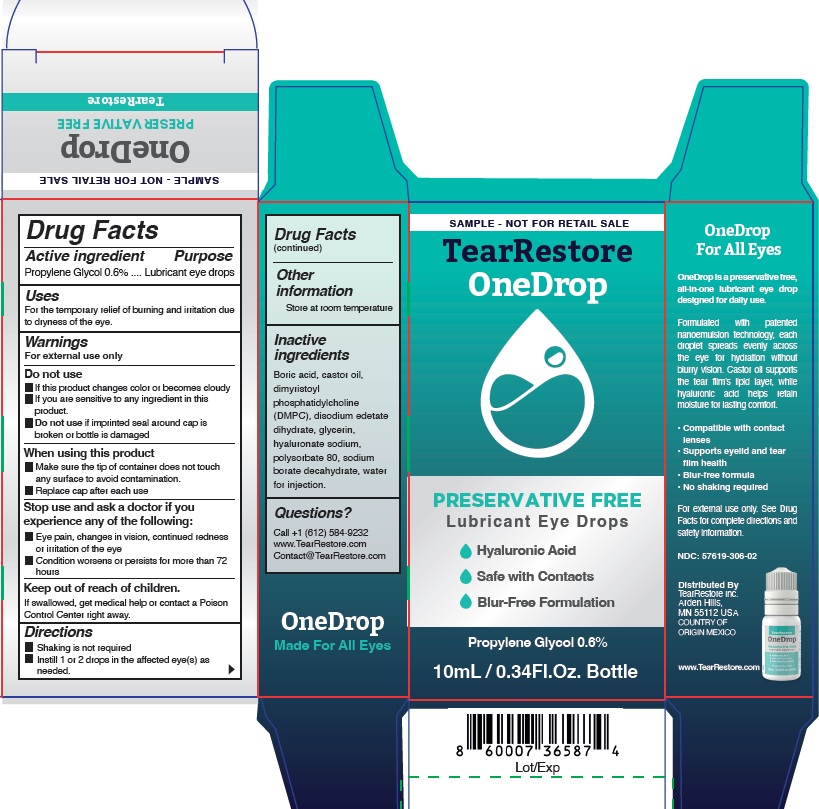 DRUG LABEL: OneDrop
NDC: 57619-306 | Form: LIQUID
Manufacturer: LABORATORIOS SOPHIA, S.A. DE C.V.
Category: otc | Type: HUMAN OTC DRUG LABEL
Date: 20250818

ACTIVE INGREDIENTS: PROPYLENE GLYCOL 0.6 g/100 mL
INACTIVE INGREDIENTS: BORIC ACID; POLYSORBATE 80; CASTOR OIL; EDETATE DISODIUM; GLYCERIN; HYALURONATE SODIUM; SODIUM BORATE; WATER; DIMYRISTOYLPHOSPHATIDYLCHOLINE, DL-

Tear Restore One Drop

Active ingredient

Propylene Glycol 0.6%

Purpose

Lubricant eye drops

Uses

For the temporary relief of burning and irritation due
to dryness of the eye.

Warnings

For external use only

Do not use

- If this product changes color or becomes cloudy
- If you are sensitive to any ingredient in this product.
- Do not use if imprinted seal around cap is broken or bottle is damaged

When using this product

- Make sure the tip of container does not touch any surface to avoid contamination.
- Replace cap after each use

Stop use and ask a doctor if you experience any of the following:

- Eye pain, changes in vision, continued redness or irritation of the eye
- Condition worsens or persists for more than 72 hours

Keep out of reach of children.

If swallowed, get medical help or contact a Poison Control Center right away.

Directions

- Shaking is not required
- Instill 1 or 2 drops in the affected eye(s) as needed.

Other information

Store at room temperature

Inactive ingredients

Boric acid, castor oil, dimyristoyl phosphatidylcholine (DMPC), disodium edetate dihydrate, glycerin,hyaluronate sodium, polysorbate 80, sodium borate decahydrate, water for injection.

Questions?

Call +1 (612) 584-9232
www.TearRestore.com
Contact@TearRestore.com

For external use only. See Drug Facs for complete directions and safety information.

NDC: 57619-306-01

Distributed By

TearRestore Inc.

Arden Hills, MN 55112 USA

Country of Origin Mexico

www.TearRestore.com

PACKAGE LABEL

TearRestore

OneDrop

PRESERVATIVE FREE

Lubricant Eye Drops

Hyaluronic Acid

Safe with Contacts
Blur-Free Formulation

Propylene Glycol 0.6%

10mL / 0.34 Fl. Oz. Bottle